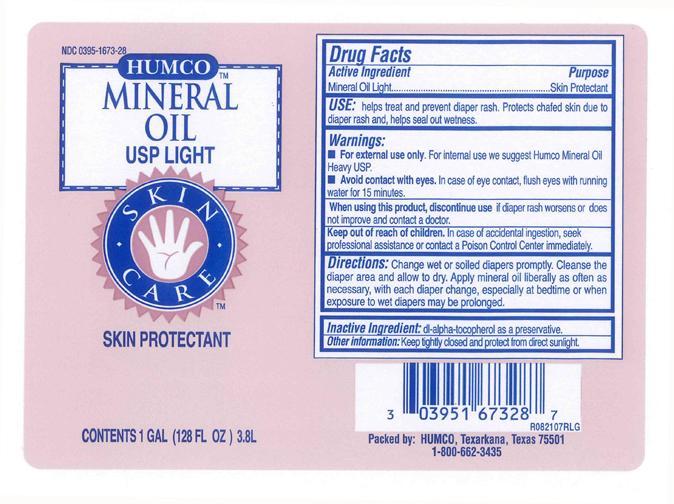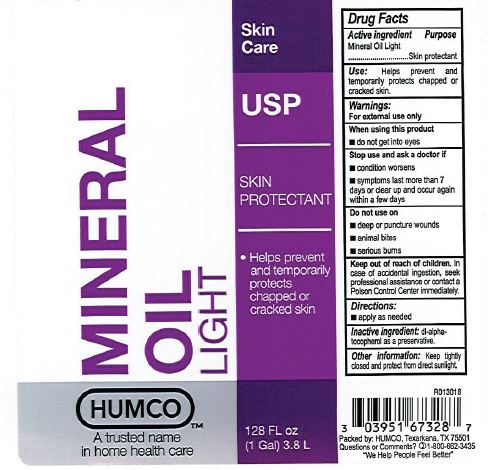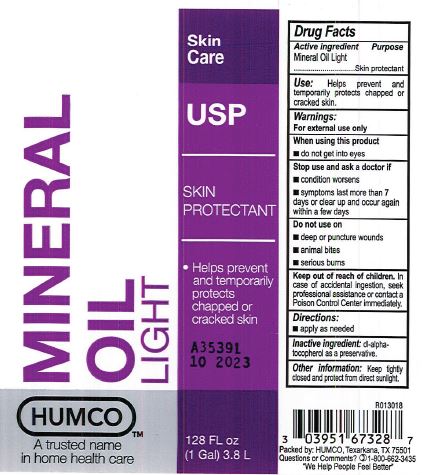 DRUG LABEL: Humco Mineral Oil Light
NDC: 0395-1673 | Form: LIQUID
Manufacturer: Humco Holding Group, Inc.
Category: otc | Type: HUMAN OTC DRUG LABEL
Date: 20231215

ACTIVE INGREDIENTS: MINERAL OIL 1000 mg/1 mL
INACTIVE INGREDIENTS: .ALPHA.-TOCOPHEROL, DL-

Humco Mineral Oil USP Light

Drug Facts

Active ingredient

Mineral Oil

Purpose

Skin Protectant

Use

Help treat and prevent diaper rash. Protects chafed skin due to diaper rash and, helps seal out wetness.

Warnings

For external use only. For internal use we suggest Humco Mineral Oil Heavy USP.

Avoid contact with eyes. In case of eye contact, flush eyes with running water for 15 minutes.

When using this product

Discontinue use if diaper rash worsens or does not improve and contact doctor.

Keep out of reach of children.

In case of accidental ingestion, seek professional assistance or contact a Poison Control Center immediately.

Directions

Change wet or soiled diapers promptly. Cleanse the diaper area and allow to dry. Apply mineral oil liberally as often as necessary, with each diapper change, especially at bed time or when exposure to wet diapers may be prolonged.

Inactive ingredient

dl-alpha tocopherol as a preservative.

Other information

Keep tightly closed and protect from direct sunlight.

Principal display panel

label